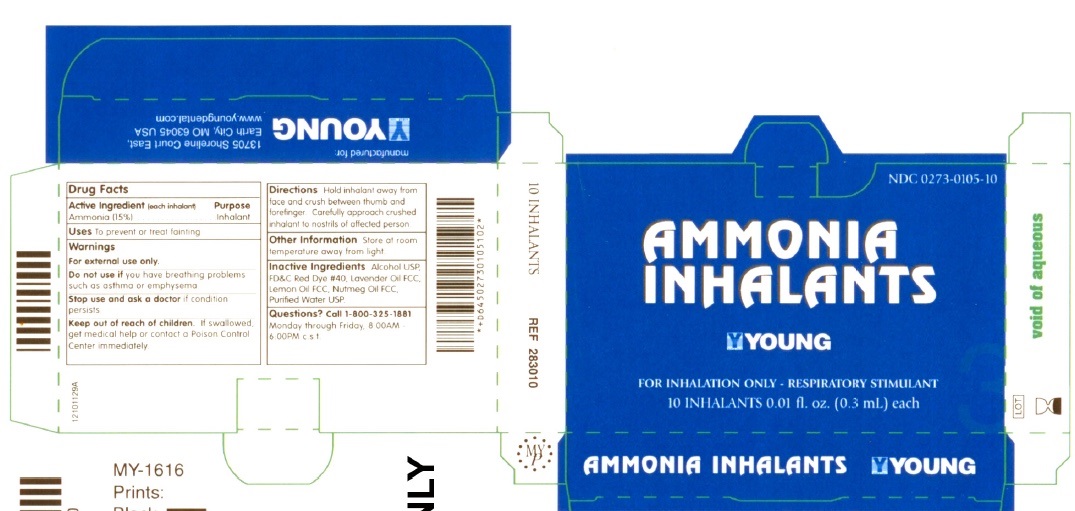 DRUG LABEL: Ammonia Inhalants
NDC: 0273-0104 | Form: INHALANT
Manufacturer: YOUNG DENTAL MANUFACTURING CO 1, LLC
Category: otc | Type: HUMAN OTC DRUG LABEL
Date: 20230103

ACTIVE INGREDIENTS: AMMONIA 0.045 g/0.3 mL
INACTIVE INGREDIENTS: ALCOHOL; LEMON OIL; LAVANDIN OIL; NUTMEG OIL; FD&C RED NO. 40; WATER

AMMONIA INHALER

Actives

Ammonia 15 percent

Purpose

Inhalant

Usage

To treat or prevent fainting.

Warnings

For External Use Only.

Stop use and ask a doctor if condition persists. Do not use if you have breathing problems such as asthma or emphysema.

Keep out of reach of children

If swallowed get medical help or contact a Poison Control Center immediately.

Dosage and Administration

Directions: Hold inhalant away from face and crush between thumb and forefinger. Carefully approach crushed inhalant to nostrils of affected person.

Inactives

Alcohol USP, FDC red dye 40, Lavender oil fcc, Lemon oil fcc, Nutmeg oil fcc, Purified water usp